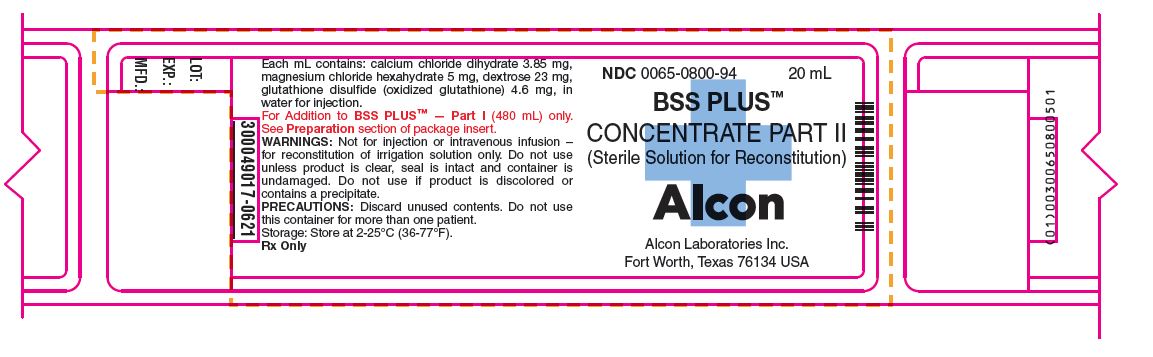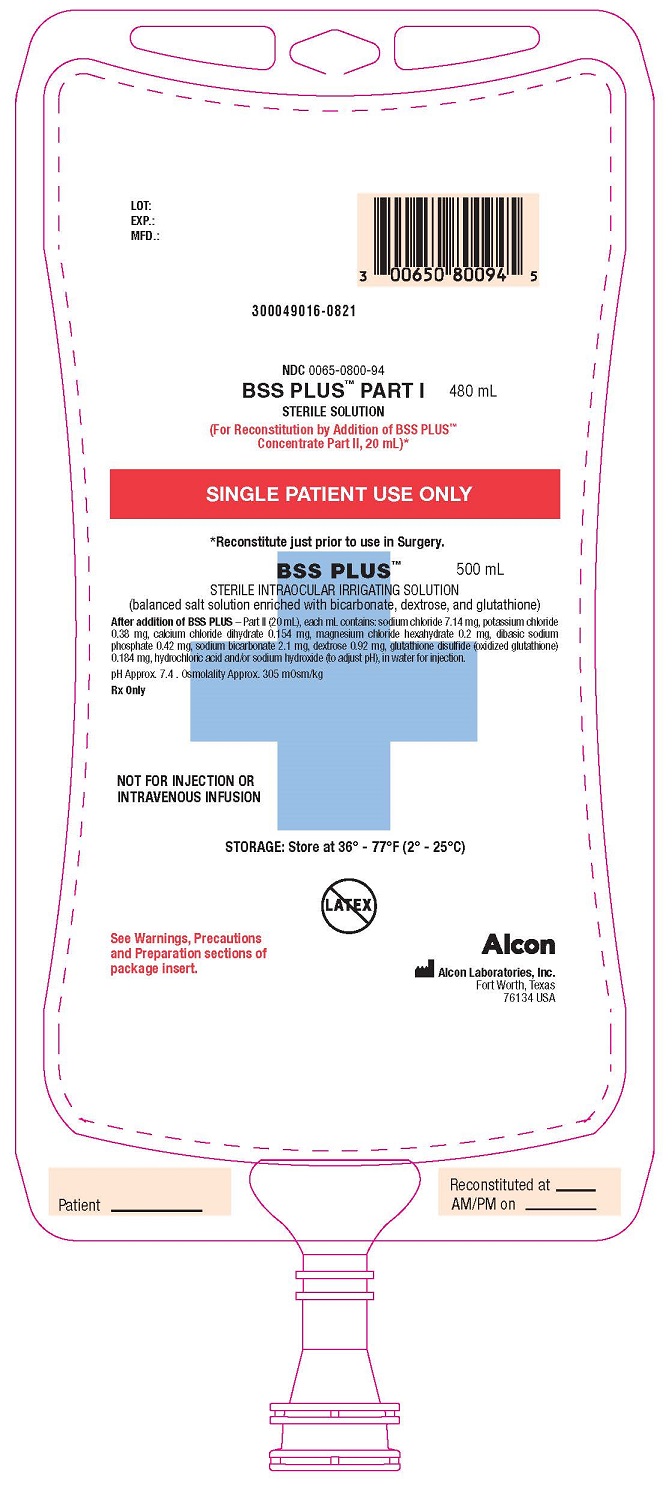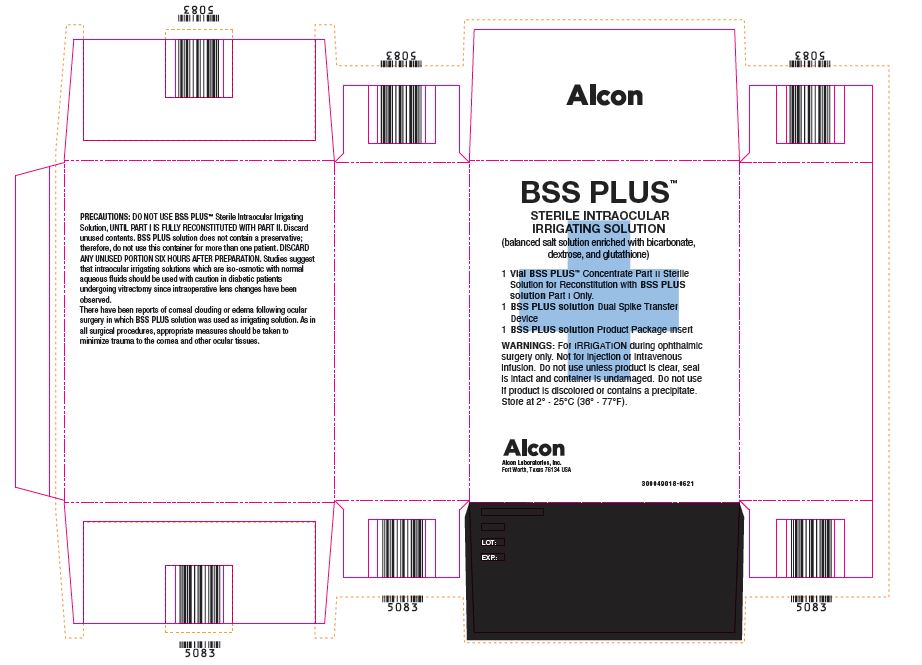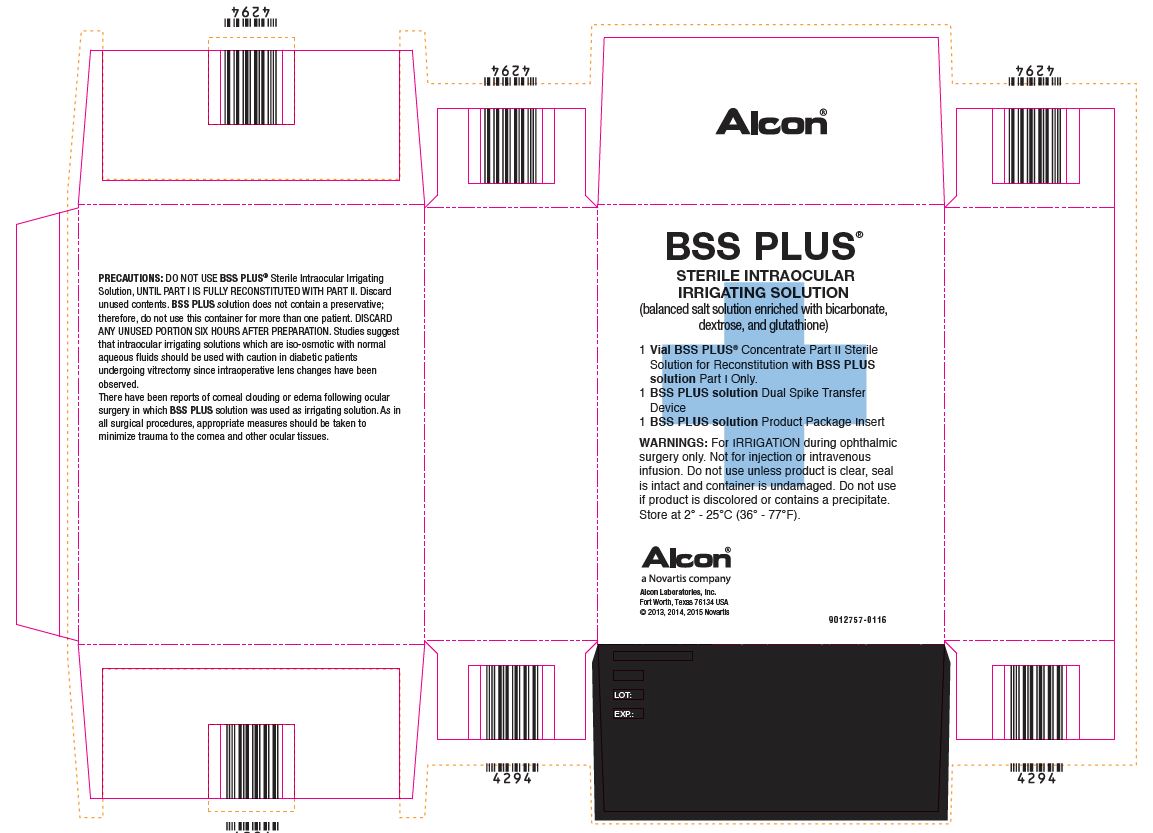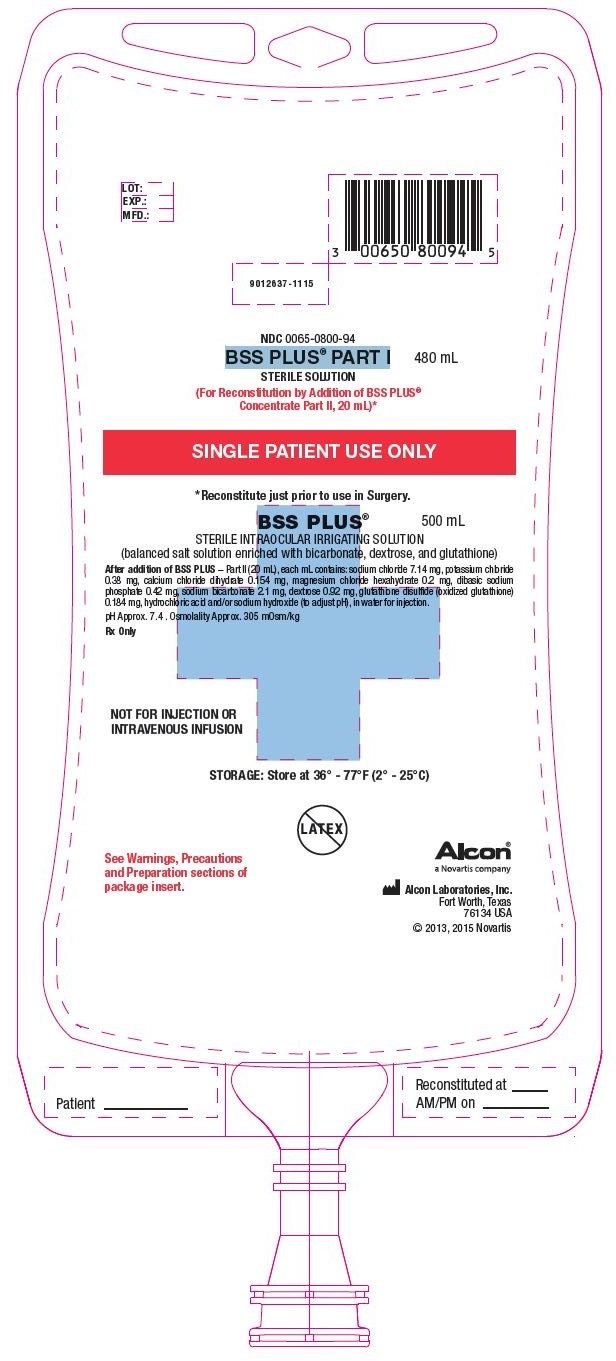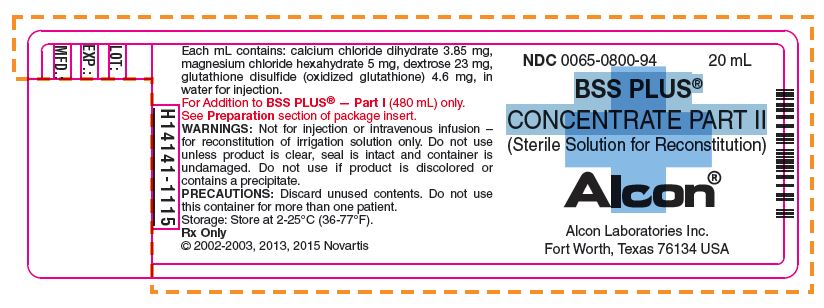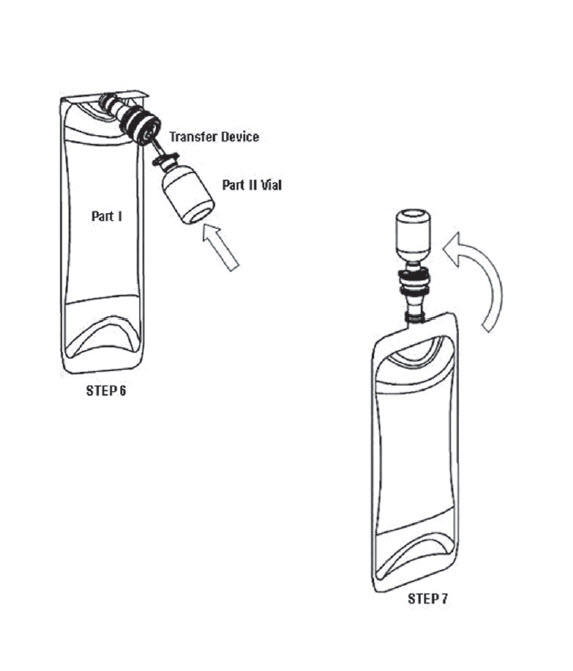 DRUG LABEL: BSS PLUS 
NDC: 0065-0800 | Form: KIT | Route: OPHTHALMIC
Manufacturer: Alcon Laboratories, Inc.
Category: prescription | Type: HUMAN PRESCRIPTION DRUG LABEL
Date: 20240125

ACTIVE INGREDIENTS: Sodium Chloride 7.44 mg/1 mL; Potassium Chloride 0.395 mg/1 mL; Sodium Phosphate, Dibasic 0.433 mg/1 mL; Sodium Bicarbonate 2.19 mg/1 mL; Calcium Chloride 3.85 mg/1 mL; Magnesium Chloride 5 mg/1 mL; Dextrose, Unspecified Form 23 mg/1 mL; Oxiglutatione 4.6 mg/1 mL
INACTIVE INGREDIENTS: Hydrochloric Acid; Sodium Hydroxide; Water; Water

BSS PLUS™
STERILE IRRIGATING SOLUTION
(balanced salt solution enriched with bicarbonate, dextrose, and glutathione)

DESCRIPTION

BSS PLUS® is a sterile intraocular irrigating solution for use during all intraocular surgical procedures, including those requiring a relatively long intraocular perfusion time (e.g., pars plana vitrectomy, phacoemulsification, extra capsular cataract extraction/lens aspiration, anterior segment reconstruction, etc.). The solution does not contain a preservative and should be prepared just prior to use in surgery.
Part I: Part I is a sterile 480 mL solution in a 500 mL single-dose bag to which the Part II concentrate is added. Each mL of Part I contains: sodium chloride 7.44 mg, potassium chloride 0.395 mg, dibasic sodium phosphate 0.433 mg, sodium bicarbonate 2.19 mg, hydrochloric acid and/or sodium hydroxide (to adjust pH), in water for injection.
Part II: Part II is a sterile concentrate in a 20 mL single-dose vial for addition to Part I. Each mL of Part II contains: calcium chloride dihydrate 3.85 mg, magnesium chloride hexahydrate 5 mg, dextrose 23 mg, glutathione disulfide (oxidized glutathione) 4.6 mg, in water for injection.
After addition of BSS PLUS solution Part II to the Part I bag, each mL of the reconstituted product contains: sodium chloride 7.14 mg, potassium chloride 0.38 mg, calcium chloride dihydrate 0.154 mg, magnesium chloride hexahydrate 0.2 mg, dibasic sodium phosphate 0.42 mg, sodium bicarbonate 2.1 mg, dextrose 0.92 mg, glutathione disulfide (oxidized glutathione) 0.184 mg, hydrochloric acid and/or sodium hydroxide (to adjust pH), in water for injection.
The reconstituted product has a pH of approximately 7.4. Osmolality is approximately 305 mOsm.

CLINICAL PHARMACOLOGY

None of the components of BSS PLUS are foreign to the eye. Human perfused cornea studies have shown BSS PLUS to be an effective irrigation solution for providing corneal detumescence and maintaining corneal endothelial integrity during intraocular perfusion. An in vivo study in rabbits has shown that BSS PLUS is more suitable than normal saline or Balanced Salt Solution for intravitreal irrigation because BSS PLUS contains the appropriate bicarbonate, pH, and ionic composition necessary for the maintenance of normal retinal electrical activity. Human in vivo studies have demonstrated BSS PLUS to be safe and effective when used during surgical procedures such as pars plana vitrectomy, phacoemulsification, cataract extraction/lens aspiration, anterior segment reconstruction. No differences have been observed between adults and pediatric patients following use of this drug product.

INDICATIONS AND USAGE:

BSS PLUS solution is indicated for use as an intraocular irrigating solution during intraocular surgical procedures involving perfusion of the eye.

CONTRAINDICATIONS

There are no specific contraindications to the use of BSS PLUS solution; however, contraindications for the surgical procedure during which BSS PLUS solution is to be used should be strictly adhered to.

WARNINGS

For IRRIGATION during ophthalmic surgery only. Not for injection or intravenous infusion. Do not use unless product is clear, seal is intact and container is undamaged. Do not use if product is discolored or contains a precipitate.

PRECAUTIONS

DO NOT USE BSS PLUS solution UNTIL PART I IS FULLY RECONSTITUTED WITH PART II. Discard unused contents. BSS PLUS does not contain a preservative; therefore, do not use this container for more than one patient. DISCARD ANY UNUSED PORTION SIX HOURS AFTER PREPARATION. Studies suggest that intraocular irrigating solutions which are iso-osmotic with normal aqueous fluids should be used with caution in diabetic patients undergoing vitrectomy since intraoperative lens changes have been observed.
There have been reports of corneal clouding or edema following ocular surgery in which BSS PLUS solution was used as an irrigating solution. As in all surgical procedures appropriate measures should be taken to minimize trauma to the cornea and other ocular tissues.

Preparation

Reconstitute BSS PLUS® Intraocular Irrigating Solution just prior to use in surgery. Follow the same strict aseptic procedures in the reconstitution of BSS PLUS as is used for intravenous additives. Remove the blue flip-off seal from the BSS PLUS Part I (480 mL) bag. Remove the blue flip-off seal from the BSS PLUS Part II (20 mL) vial. Clean and disinfect the rubber stoppers on both containers by using sterile alcohol wipes. Transfer the contents of the Part II vial to the Part I bag using a BSS PLUS Vacuum Transfer Device (provided). An alternative method of solution transfer may be accomplished by using a 20 mL syringe to remove the Part II solution from the vial and transferring exactly 20 mL to the Part I container through the outer target area of the rubber stopper. An excess volume of Part II is provided in each vial. Gently agitate the contents to mix the solution. Place a sterile cap on the bag. Remove the tear-off portion of the label. Record the time and date of reconstitution and the patient's name on the bag label.

GERIATRIC USE

No overall differences in safety or effectiveness have been observed between elderly and younger patients.

ADVERSE REACTIONS

Postoperative inflammatory reactions as well as incidents of corneal edema and corneal decompensation have been reported. Their relationship to the use of BSS PLUS solution has not been established.

DOSAGE AND ADMINISTRATION

The solution should be used according to the standard technique employed by the operating surgeon. Use an administration set with an air-inlet in the plastic spike since the bag does not contain a separate airway tube. Follow the directions for the particular administration set to be used. Insert the spike aseptically into the bag through the center target area of the rubber stopper. Allow the fluid to flow to remove air from the tubing before intraocular irrigation begins.

HOW SUPPLIED

BSS PLUS solution is supplied in two packages for reconstitution prior to use: a 500 mL bag containing 480 mL (Part I) and a 20 mL glass vial (Part II); both using grey butyl stoppers and aluminum seals. See the PRECAUTIONS section regarding reconstitution of the solution.
NDC 0065-0800-94

STORAGE

Store Part I and Part II at 2˚C to 25˚C (36°F to 77° F). Discard prepared solution after six hours.

Revised: April 2023

Alcon
Distributed by:
Alcon Laboratories, Inc.
Fort Worth, Texas 76134 USA
© 2023 Alcon Inc.

RECONSTITUTION INSTRUCTIONS
DIRECTIONS: Use Aseptic Technique

1. Remove the BSS PLUS™ solution Part I (480 mL) bag from the clear overwrap. Remove the blue flip-off seal from the BSS PLUS solution Part II (20 mL) vial. Prepare the stoppers on both parts by using sterile alcohol wipes.
2. Peel open a BSS PLUS solution Dual-Spike Transfer Device package (supplied) and remove the sterile transfer spike. NOTE: This device is vented permitting air to enter vial during solution transfer, thereby preventing the creation of a vacuum inside the vial.
3. Remove protector from the white plastic piercing pin of the Dual-Spike Transfer Device.
4. Firmly grasp device from behind the flange and insert the white plastic piercing pin into the upright rubber stopper of the BSS PLUS solution Part II (20 mL) vial.
5. Remove guard from filter needle. Firmly grasp vial in the palm of one hand and with thumb and index finger, hold plastic flange against top of vial.
6. Hold the vial in the upright position, incline and immediately insert the transfer device into the center target of rubber stopper of the BSS PLUS solution Part I (480 mL) bag. (See illustration.) NOTE: Do not invert Part II (20mL) vial before or during spiking of the BSS PLUS solution Part I bag rubber stopper, until ready to initiate transfer.
7. Invert vial to initiate the transfer of Part II into Part I. If transfer does not occur immediately, gentle manipulation of the bag can initiate transfer. NOTE: An excess amount of BSS PLUS solution Part II is provided in each vial. A non-transferred solution residual of approximately 0.3 mL can be expected to remain in the vial.
8. Immediately remove vial (with spike attached) from the BSS PLUS solution Part I container and discard it after solution transfer has been completed.
9. Place a sterile safety cap over the rubber stopper of Part I if the solution is not going to be used immediately. Mix the solution gently until uniform. Record the patient’s name and the date and time of reconstitution. BSS PLUS solution is now ready for use.

CAUTION: Reconstituted BSS PLUS solution must be used within six hours of mixing.
Discard any solution which has aged beyond that time. Never use the same bag of BSS PLUS solution on more than one patient.
Alternative Transfer Method
If preferred, the contents of the BSS PLUS Part II component may be aspirated with an 18-gauge cannula attached to a 20 mL syringe and then transferred into the Part I bag.

Alcon
Distributed by:
Alcon Laboratories, Inc.
Fort Worth, Texas 76134 USA
© 2023 Alcon Inc.

PRINCIPAL DISPLAY PANEL

NDC 0065-0800-94
BSS PLUS™ PART I 480 mL
STERILE SOLUTION
(For Reconstitution by Addition of BSS PLUS™
Concentrate Part II, 20 mL)*
SINGLE PATIENT USE ONLY
*Reconstitute just prior to use in Surgery.
BSS PLUS™ 500 mL
STERILE INTRAOCULAR IRRIGATING SOLUTION
(balanced salt solution enriched with bicarbonate, dextrose, and glutathione)
After addition of BSS PLUS – Part II (20 mL), each mL contains: sodium chloride 7.14 mg, potassium chloride 0.38 mg, calcium chloride dihydrate 0.154 mg, magnesium chloride hexahydrate 0.2 mg, dibasic sodium phosphate 0.42 mg, sodium bicarbonate 2.1 mg, dextrose 0.92 mg, glutathione disulfide (oxidized glutathione) 0.184 mg, hydrochloric acid and/or sodium hydroxide (to adjust pH), in water for injection.
pH Approx. 7.4. Osmolality Approx. 305 mOsm/kg
Rx Only
NOT FOR INJECTION OR
INTRAVENOUS INFUSION
STORAGE: Store at 36° - 77°F (2° - 25°C)
See Warnings, Precautions
and Preparation sections of
package insert.
Alcon
Alcon Laboratories, Inc.
Fort Worth, Texas 76134 USA
LOT:
EXP.:
MFD.:
300049016-0821
Patient____________________
Reconstituted at_____________
AM/PM on_________________

NDC 0065-0800-94
BSS PLUS® PART I 480 mL
STERILE SOLUTION
(For Reconstitution by Addition of BSS PLUS®
Concentrate Part II, 20 mL)*
SINGLE PATIENT USE ONLY
*Reconstitute just prior to use in Surgery.
BSS PLUS* 500 mL
STERILE INTRAOCULAR IRRIGATING SOLUTION
(balanced salt solution enriched with bicarbonate, dextrose, and glutathione)
After addition of BSS PLUS – Part II (20 mL), each mL contains: sodium chloride 7.14 mg, potassium chloride 0.38 mg, calcium chloride dihydrate 0.154 mg, magnesium chloride hexahydrate 0.2 mg, dibasic sodium phosphate 0.42 mg, sodium bicarbonate 2.1 mg, dextrose 0.92 mg, glutathione disulfide (oxidized glutathione) 0.184 mg, hydrochloric acid and/or sodium hydroxide (to adjust pH), in water for injection.
pH Approx. 7.4. Osmolality Approx. 305 mOsm/kg
Rx Only
NOT FOR INJECTION OR
INTRAVENOUS INFUSION
STORAGE: Store at 36° - 77°F (2° - 25°C)
See Warnings, Precautions
and Preparation sections of
package insert.
Alcon®
a Novartis company
Alcon Laboratories, Inc.
Fort Worth, Texas 76134 USA
© 2013, 2015 Novartis
LOT:
EXP.:
MFD.:
9012637-1115
Patient____________________
Reconstituted at_____________
AM/PM on_________________

NDC 0065-0800-94 20mL
BSS PLUS™
CONCENTRATE PART II
(Sterile Solution for Reconstitution)
Alcon
Alcon Laboratories Inc.
Fort Worth, Texas 76134 USA
Each mL contains: calcium chloride dihydrate 3.85 mg, magnesium chloride hexahydrate 5 mg, dextrose 23 mg, glutathione disulfide (oxidized glutathione) 4.6 mg, in water for injection.
For Addition to BSS PLUS™ — Part I (480 mL) only.
See Preparation section of package insert.
WARNINGS: Not for injection or intravenous infusion – for reconstitution of irrigation solution only. Do not use unless product is clear, seal is intact and container is undamaged. Do not use if product is discolored or contains a precipitate.
PRECAUTIONS: Discard unused contents. Do not use this container for more than one patient.
Storage: Store at 2-25°C (36-77°F).
Rx Only
300049017-0621
LOT:
EXP.:
MFD.:

NDC 0065-0800-94 20mL
BSS PLUS®
CONCENTRATE PART II
(Sterile Solution for Reconstitution)
Alcon®
Alcon Laboratories Inc.
Fort Worth, Texas 76134 USA
Each mL contains: calcium chloride dihydrate 3.85 mg, magnesium chloride hexahydrate 5 mg, dextrose 23 mg, glutathione disulfide (oxidized glutathione) 4.6 mg, in water for injection.
For Addition to BSS PLUS® — Part I (480 mL) only.
See Preparation section of package insert.
WARNINGS: Not for injection or intravenous infusion – for reconstitution of irrigation solution only. Do not use unless product is clear, seal is intact and container is undamaged. Do not use if product is discolored or contains a precipitate.
PRECAUTIONS: Discard unused contents. Do not use this container for more than one patient.
Storage: Store at 2-25°C (36-77°F).
Rx Only
© 2002-2003, 2013, 2015 Novartis
H14141-1115
LOT:
EXP.:
MFD.:

BSS PLUS™
STERILE INTRAOCULAR
IRRIGATING SOLUTION
(balanced salt solution enriched with bicarbonate, dextrose, and glutathione)
1 Vial BSS PLUS® Concentrate Part II Sterile Solution for Reconstitution with BSS PLUS solution Part 1 Only
1 BSS PLUS solution Dual Spike Transfer Device
1 BSS PLUS solution Product Package Insert
WARNINGS: For IRRIGATION during ophthalmic surgery only. Not for injection or intravenous infusion. Do not use unless product is clear, seal is intact and container is undamaged. Do not use if product is discolored or contains a precipitate.
Store at 2° - 25°C (36° - 77°F).
Alcon
Alcon Laboratories, Inc.
Fort Worth, Texas 76134 USA
300049018-0621
PRECAUTIONS: DO NOT USE BSS PLUS* Sterile Intraocular Irrigating Solution, UNTIL PART I IS FULLY RECONSTITUTED WITH PART II. Discard unused contents. BSS PLUS solution does not contain a preservative; therefore, do not use this container for more than one patient. DISCARD ANY UNUSED PORTION SIX HOURS AFTER PREPARATION. Studies suggest that intraocular irrigating solutions which are iso-osmotic with normal aqueous fluids should be used with caution in diabetic patients undergoing vitrectomy since intraoperative lens changes have been observed.
There have been reports of corneal clouding or edema following ocular surgery in which BSS PLUS solution was used as irrigating solution. As in all surgical procedures, appropriate measures should be taken to minimize trauma to the cornea and other ocular tissues.
LOT:
EXP:
MFD:

BSS PLUS®
STERILE INTRAOCULAR
IRRIGATING SOLUTION
(balanced salt solution enriched with bicarbonate, dextrose, and glutathione)
1 Vial BSS PLUS® Concentrate Part II Sterile Solution for Reconstitution with BSS PLUS solution Part 1 Only
1 BSS PLUS solution Dual Spike Transfer Device
1 BSS PLUS solution Product Package Insert
WARNINGS: For IRRIGATION during ophthalmic surgery only. Not for injection or intravenous infusion. Do not use unless product is clear, seal is intact and container is undamaged. Do not use if product is discolored or contains a precipitate.
Store at 2° - 25°C (36° - 77°F).
Alcon®
a Novartis company
Alcon Laboratories, Inc.
Fort Worth, Texas 76134 USA
© 2013, 2014, 2015 Novartis
9012757-0116
PRECAUTIONS: DO NOT USE BSS PLUS* Sterile Intraocular Irrigating Solution, UNTIL PART I IS FULLY RECONSTITUTED WITH PART II. Discard unused contents. BSS PLUS solution does not contain a preservative; therefore, do not use this container for more than one patient. DISCARD ANY UNUSED PORTION SIX HOURS AFTER PREPARATION. Studies suggest that intraocular irrigating solutions which are iso-osmotic with normal aqueous fluids should be used with caution in diabetic patients undergoing vitrectomy since intraoperative lens changes have been observed.
There have been reports of corneal clouding or edema following ocular surgery in which BSS PLUS solution was used as irrigating solution. As in all surgical procedures, appropriate measures should be taken to minimize trauma to the cornea and other ocular tissues.
LOT:
EXP:
MFD: